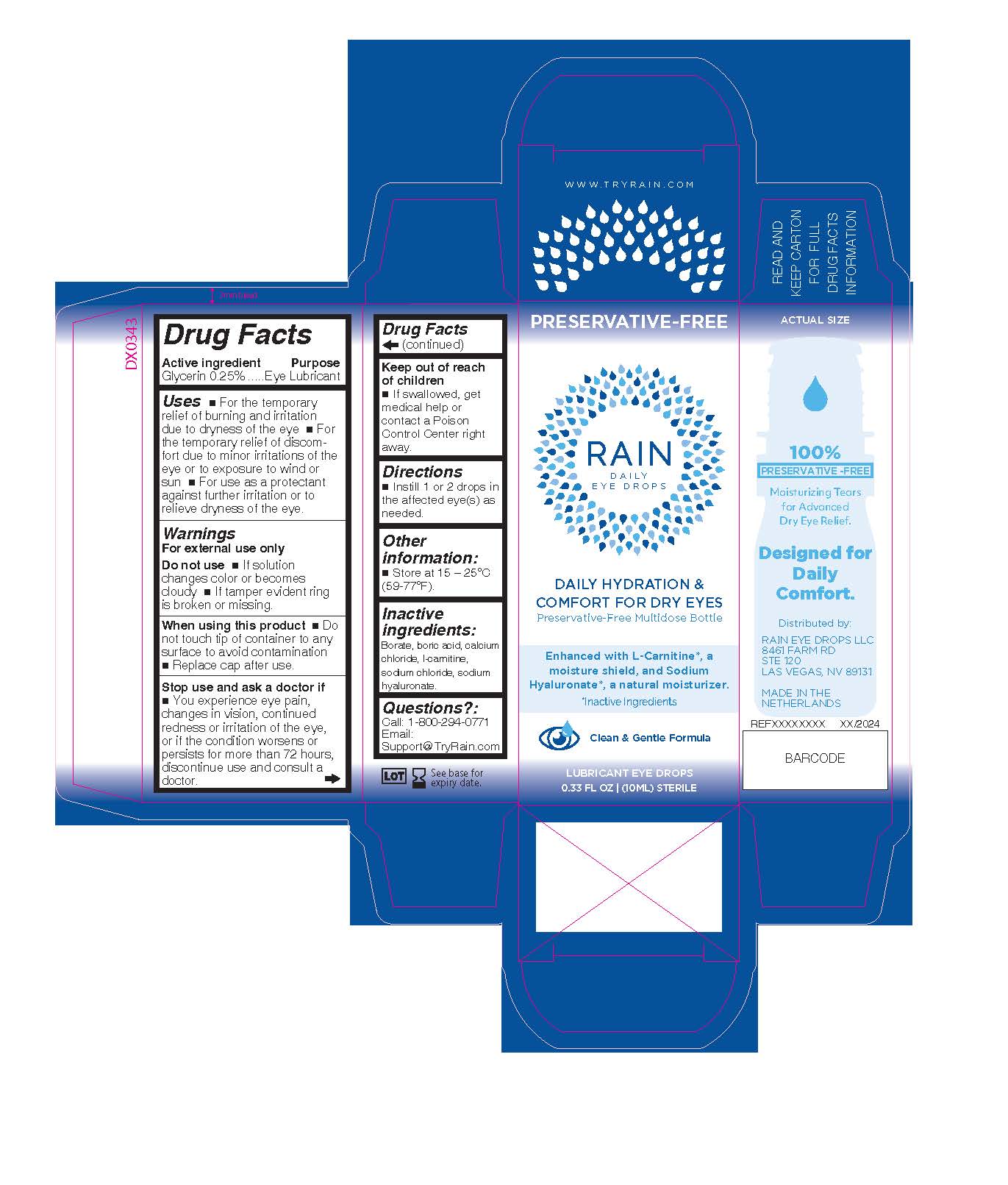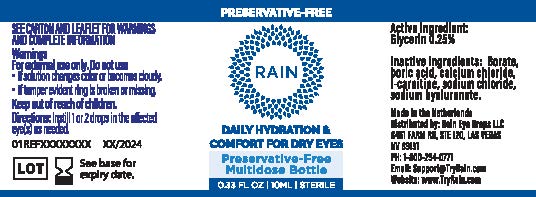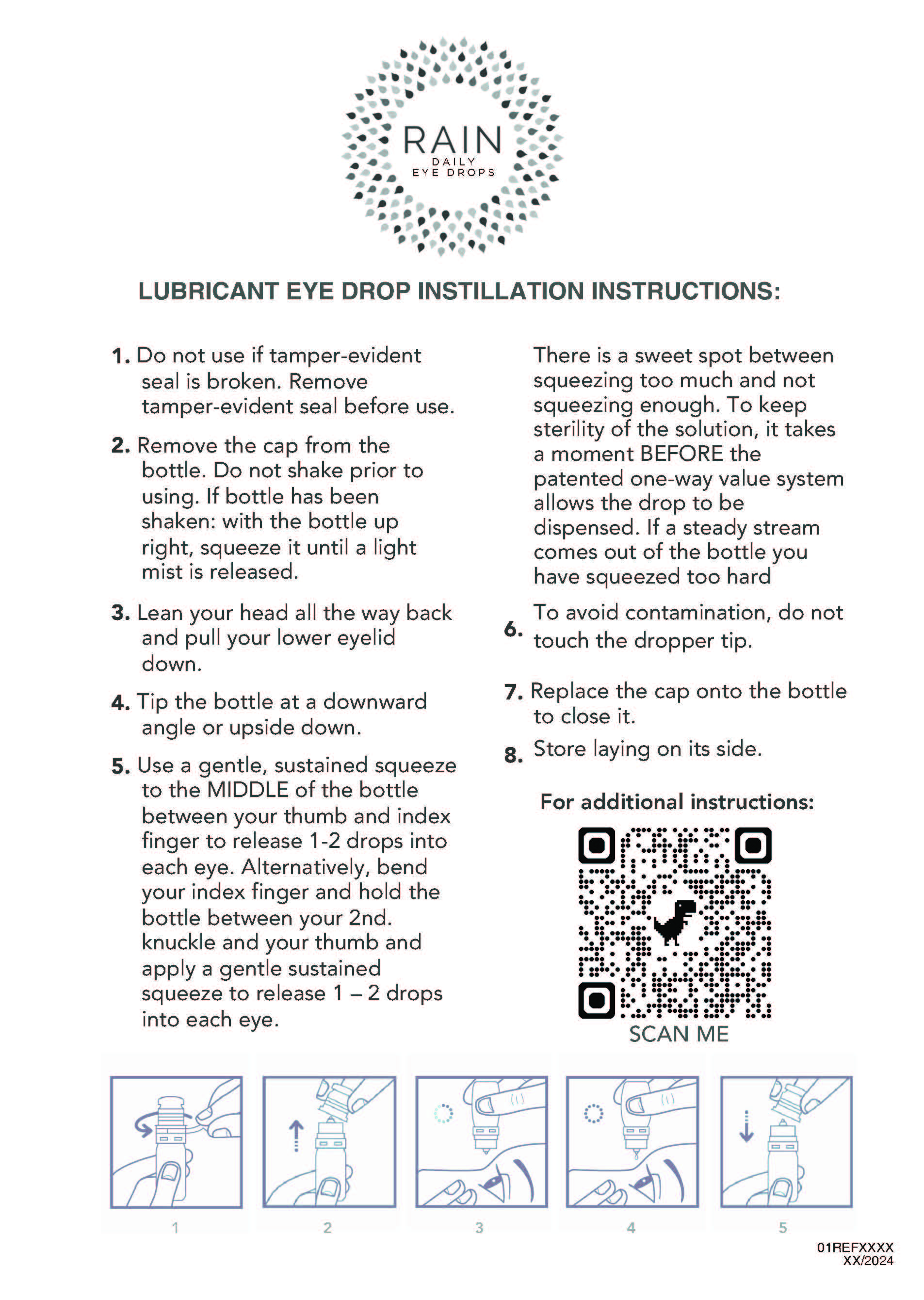 DRUG LABEL: Rain Daily Hydration and Comfort For Dry Eyes
NDC: 79662-003 | Form: SOLUTION/ DROPS
Manufacturer: Rain Eye Drops, LLC
Category: otc | Type: HUMAN OTC DRUG LABEL
Date: 20251123

ACTIVE INGREDIENTS: GLYCERIN 2.5 mg/1 mL
INACTIVE INGREDIENTS: CALCIUM CHLORIDE; DL-CARNITINE; SODIUM CHLORIDE; BORATE ION; BORIC ACID; SODIUM HYALURONATE

Rain Daily Hydration and Comfort For Dry Eyes

ACTIVE INGREDIENT

Glycerin 0.25%

PURPOSE

Glycerin............Lubricant

INDICATIONS AND USAGE

Uses  For the temporary

relief of burning and irritation
due to dryness of the eye  For
the temporary relief of discomfort
due to minor irritations of the
eye or to exposure to wind or
sun  For use as a protectant
against further irritation or to
relieve dryness of the eye.

Warnings

For external use only.

Do not use  If solution
changes color or becomes
cloudy  If tamper evident ring
is broken or missing.
When using this product  Do
not touch tip of container to any
surface to avoid contamination
 Replace cap after use.
Stop use and ask a doctor if
 You experience eye pain,
changes in vision, continued
redness or irritation of the eye,
or if the condition worsens or
persists for more than 72 hours,
discontinue use and consult a
doctor.

Keep out of reach of children. If accidentally swallowed, get medical help or contact a Poison Control Center right away.

Directions
 Instill 1 or 2 drops in
the affected eye(s) as
needed.

Other
information:
 Store at 15 – 25°C
(59-77°F).

Inactive ingredients:
Borate, boric acid, calcium
chloride, l-carnitine,
sodium chloride, sodium
hyaluronate.